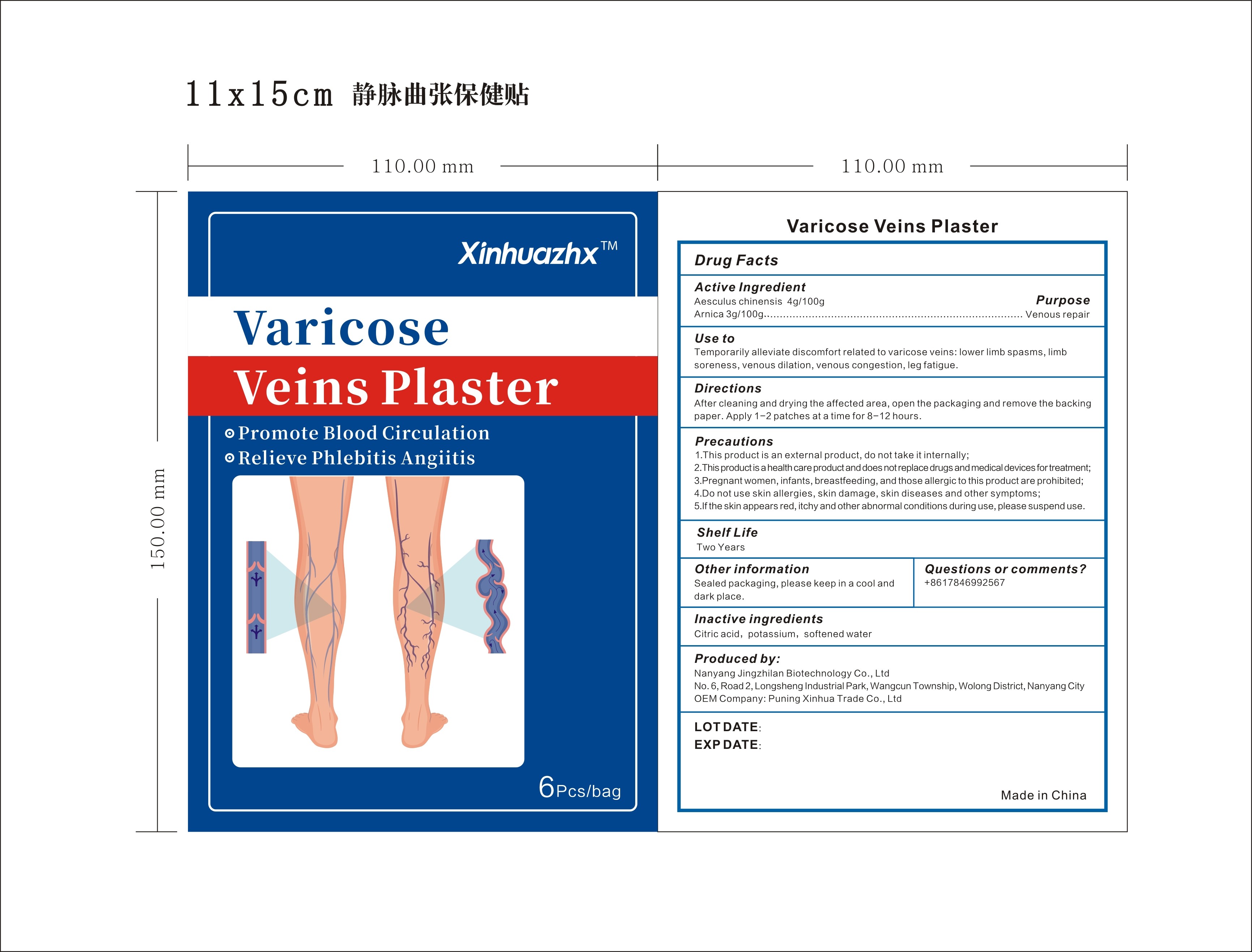 DRUG LABEL: Xinhuazhx Varicoce Veins Plaster
NDC: 83702-017 | Form: PATCH
Manufacturer: Puning Xinhua Trade Co., Ltd.
Category: otc | Type: HUMAN OTC DRUG LABEL
Date: 20231025

ACTIVE INGREDIENTS: AESCULUS CHINENSIS WHOLE 4 g/100 g; ARNICA CORDIFOLIA WHOLE 3 g/100 g
INACTIVE INGREDIENTS: POTASSIUM SORBATE; CITRIC ACID MONOHYDRATE; WATER

Xinhuazhx Varicoce Veins Plaster-83702-017-12

Active ingredient: Aesculus chinensis 4g/100g, Arnica 3g/100g

Purpose: Venous repair

INDICATIONS AND USAGE

Use to: Temporarily alleviate discomfort related to varicose veins: lower limb spasms, limb soreness, venous dilation, venous congestion, leg fatigue.

DOSAGE AND ADMINISTRATION

Directions: After cleaning and drying the affected area, open the packaging and remove the backing paper. Apply 1-2 patches at a time for 8-12 hours.

WARNINGS

Precautions:
1.This product is an external product, do not take it internally;
2.This product is a health care product and does not replace drugs and medical devices fortreatment;
3.Pregnant women, infants, breastfeeding, and those allergic to this product are prohibited;
4.Do not use skin allergies, skin damage, skin diseases and other symptoms;
5.If the skin appears red, itchy and other abnormal conditions during use, please suspend use.

Questions or comments? +8617846992567

Inactive Ingredients: Citric acid, potassium, softened water

Other information:Sealed packaging, please keep in a cool and dark place.

Produced by:
Nanyang Jingzhilan Biotechnology Co., Ltd
No.6,Road 2,Longsheng IndustrialPark,Wangcun Township, Wolong District,Nanyang City
OEM Company:Puning Xinhua Trade Co.,Ltd

Made in China

KEEP OUT OF REACH OF CHILDREN

Same as WARNINGS SECTION

Label